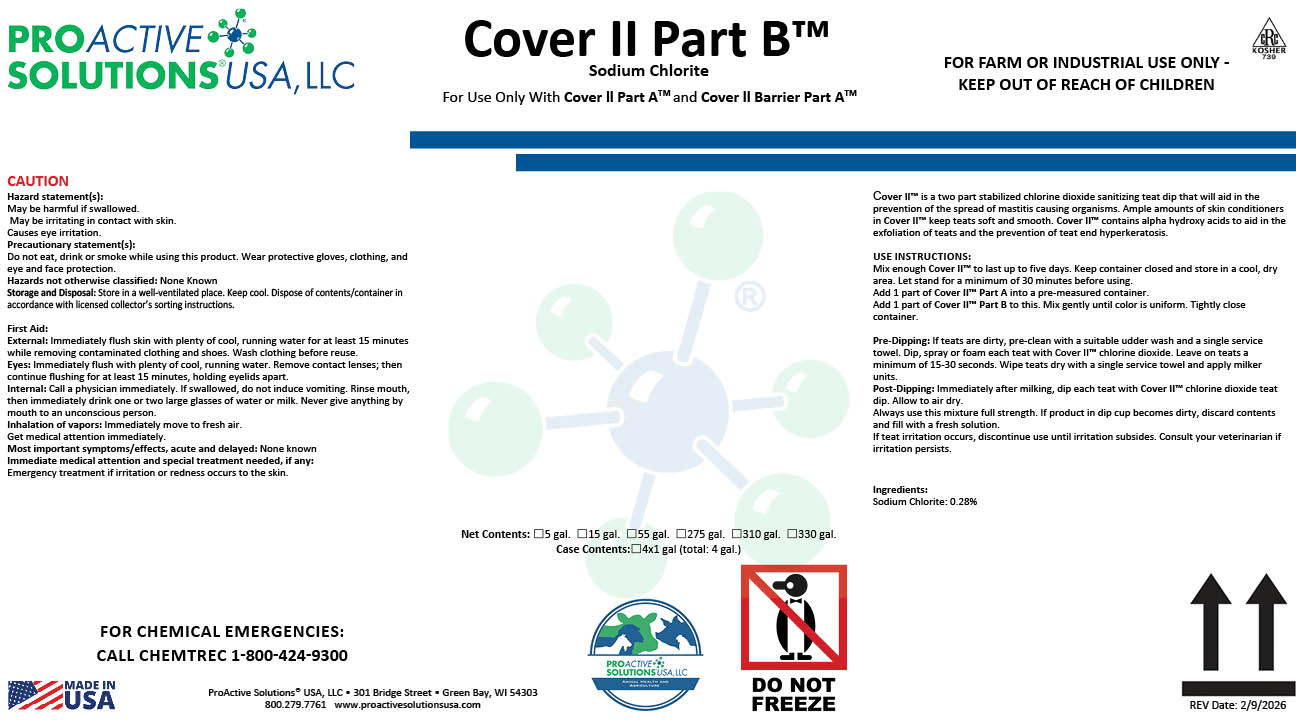 DRUG LABEL: Cover II Part B
NDC: 63927-4112 | Form: LIQUID
Manufacturer: ProActive Solutions USA, LLC
Category: animal | Type: OTC ANIMAL DRUG LABEL
Date: 20260210

ACTIVE INGREDIENTS: SODIUM CHLORITE 1.1 kg/100 kg

Cover II Part B

Cover II Part B

Cover ll Part B™
For Use Only With Cover II Part ATM Activator And Skin Conditioning Package
FOR FARM OR INDUSTRIAL USE ONLY - KEEP OUT OF REACH OF CHILDREN
FOR CHEMICAL EMERGENCIES:
CALL CHEMTREC 1-800-424-9300
Sodium Chlorite
Caution:
Hazard statement(s): May be harmful if swallowed. May be irritating in contact with skin. Causes eye irritation.
Precautionary statement(s): Do not eat, drink or smoke while using this product. Wear protective gloves, clothing, and eye and face protection.
Hazards not otherwise classified: None Known
Storage and Disposal: Store in a well-ventilated place. Keep cool. Dispose of contents/container in accordance with licensed collector’s sorting instructions.
First Aid:
External: Immediately flush skin with plenty of cool, running water for at least 15 minutes while removing contaminated clothing and shoes. Wash clothing before reuse.
Eyes: Immediately flush with plenty of cool, running water. Remove contact lenses; then continue flushing for at least 15 minutes, holding eyelids apart.
Internal: Call a physician immediately. If swallowed, do not induce vomiting. Rinse mouth, then immediately drink one or two large glasses of water or milk. Never give anything by mouth to an unconscious person.
Inhalation of vapors: Immediately move to fresh air.
Get medical attention immediately.
Most important symptoms/effects, acute and delayed: None known
Immediate medical attention and special treatment needed, if any:
Emergency treatment if irritation or redness occurs to the skin.
ProActive Solutions® USA, LLC • 301 Bridge Street • Green Bay, WI 54303
800.279.7761 www.proactivesolutionsusa.com
Cover II™ is a two part stabilized chlorine dioxide sanitizing teat dip that will aid in the prevention of the spread of mastitis causing organisms. Ample amounts of skin conditioners in Cover II™ keep teats soft and smooth. Cover II™ contains alpha hydroxy acids to aid in the exfoliation of teats and the prevention of teat end hyperkeratosis.
USE INSTRUCTIONS:
Mix enough Cover II™ to last up to five days. Keep container closed and store in a cool, dry area. Let stand for a minimum of 30 minutes before using.
Add 1 part of Cover II™ Part A into a pre-measured container.
Add 1 part of Cover II™ Part B to this. Mix gently until color is uniform. Tightly close container.
Pre-Dipping: If teats are dirty, pre-clean with a suitable udder wash and a single service towel. Dip, spray or foam each teat with Cover II™ chlorine dioxide. Leave on teats a minimum of 15-30 seconds. Wipe teats dry with a single service towel and apply milker units.
Post-Dipping: Immediately after milking, dip each teat with Cover II™ chlorine dioxide teat dip. Allow to air dry.
Always use this mixture full strength. If product in dip cup becomes dirty, discard contents and fill with a fresh solution.
If teat irritation occurs, discontinue use until irritation subsides. Consult your veterinarian if irritation persists.

Ingredients:
Sodium Chlorite: 0.28%